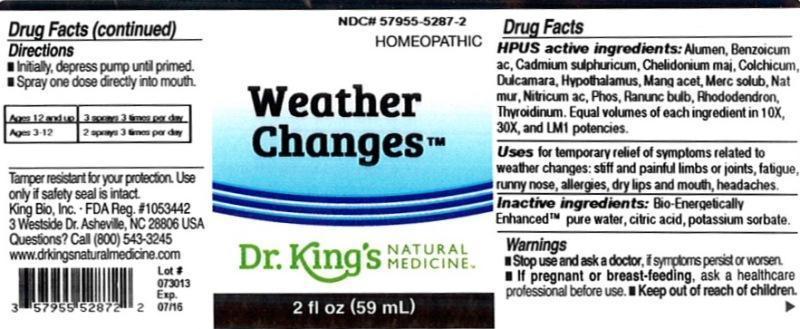 DRUG LABEL: Weather Changes
NDC: 57955-5287 | Form: LIQUID
Manufacturer: King Bio Inc.
Category: homeopathic | Type: HUMAN OTC DRUG LABEL
Date: 20130730

ACTIVE INGREDIENTS: POTASSIUM ALUM 10 [hp_X]/59 mL; BENZOIC ACID 10 [hp_X]/59 mL; CADMIUM SULFATE 10 [hp_X]/59 mL; CHELIDONIUM MAJUS 10 [hp_X]/59 mL; COLCHICUM AUTUMNALE BULB 10 [hp_X]/59 mL; SOLANUM DULCAMARA TOP 10 [hp_X]/59 mL; BOS TAURUS HYPOTHALAMUS 10 [hp_X]/59 mL; MANGANESE ACETATE TETRAHYDRATE 10 [hp_X]/59 mL; MERCURIUS SOLUBILIS 10 [hp_X]/59 mL; SODIUM CHLORIDE 10 [hp_X]/59 mL; NITRIC ACID 10 [hp_X]/59 mL; PHOSPHORUS 10 [hp_X]/59 mL; RANUNCULUS BULBOSUS 10 [hp_X]/59 mL; RHODODENDRON AUREUM LEAF 10 [hp_X]/59 mL; THYROID, UNSPECIFIED 10 [hp_X]/59 mL
INACTIVE INGREDIENTS: WATER; CITRIC ACID MONOHYDRATE; POTASSIUM SORBATE

Weather Change™

Drug Facts

____________________________________________________________________________________________________________

HPUS active ingredients: Alumen, Benzoicum acidum, Cadmium sulphuricum, Chelidonium majus, Colchicum autumnale, Dulcamara, Hypothalamus, Manganum aceticum, Mercurius solubilis, Natrum muriaticum, Nitricum acidum, Phosphorus, Ranunculus bulbosus, Rhododendron chrysanthum, Thyroidinum. Equal volumes of each ingredient in 10X, 30X and LM1 potencies.

INDICATIONS AND USAGE

Uses for temporary relief of symptoms related to weather changes:

- Stiff and painful limbs or joints
- fatigue
- runny nose
- allergies
- dry lips and mouth
- headaches

INACTIVE INGREDIENT

Inactive ingredients: Bio-Energetically Enhanced pure water base, citric acid, potassium sorbate.

Warnings

- Stop use and ask your doctor if symptoms persist or worsen.
- If pregnant or breast-feeding, ask a healthcare professional before use.

- Keep out of reach of children.

Directions:

- Initially, depress pump until primed.
- Spray one dose directly into mouth.

Ages 12 and up | 3 sprays 3 times per day
Ages 3-12 | 2 sprays 3 times per day

OTHER SAFETY INFORMATION

Tamper resistant for your protection. Use only if safety seal is intact.

PURPOSE

Uses for temporary relief of symptoms related to weather changes: stiff and painful limbs or joints, fatigue, runny nose, allergies, dry lips and mouth, headaches.